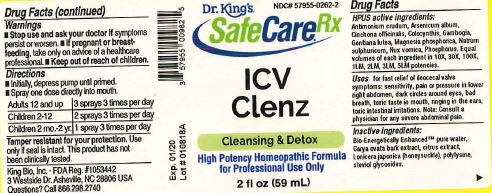 DRUG LABEL: ICV Clenz
NDC: 57955-0262 | Form: LIQUID
Manufacturer: King Bio Inc.
Category: homeopathic | Type: HUMAN OTC DRUG LABEL
Date: 20180209

ACTIVE INGREDIENTS: ANTIMONY TRISULFIDE 10 [hp_X]/59 mL; ARSENIC TRIOXIDE 10 [hp_X]/59 mL; CINCHONA OFFICINALIS BARK 10 [hp_X]/59 mL; CITRULLUS COLOCYNTHIS FRUIT PULP 10 [hp_X]/59 mL; GAMBOGE 10 [hp_X]/59 mL; GENTIANA LUTEA ROOT 10 [hp_X]/59 mL; MAGNESIUM PHOSPHATE, DIBASIC TRIHYDRATE 10 [hp_X]/59 mL; SODIUM SULFATE 10 [hp_X]/59 mL; STRYCHNOS NUX-VOMICA SEED 10 [hp_X]/59 mL; PHOSPHORUS 10 [hp_X]/59 mL
INACTIVE INGREDIENTS: WATER; CARYA OVATA BARK; CITRUS BIOFLAVONOIDS; LONICERA JAPONICA FLOWER; POLYEPSILON-LYSINE (4000 MW); REBAUDIOSIDE A

ICV Clenz™

HPUS active ingredients:

Antimonium crudum, Arsenicum album, Cinchona officinalis, Colocynthis, Gambogia, Gentiana lutea, Magnesia phosphorica, Natrum sulphuricum, Nux vomica, Phosphorus. Equal volumes of each ingredient in 10X, 30X, 100X, 1LM, 2LM, 3LM, 5LM potencies.

INDICATIONS AND USAGE

Uses for fast relief of ileocecal valve symptoms: sensitivity, pain or pressure in lower right abdomen, dark circles around eyes, bad breath, toxic taste in mouth, ringing in the ears, toxic intestinal irritations.

Note: Consult a physician for any severe abdominal pain.

Inactive Ingredients:

Bio-Energetically Enhanced™ pure water, Carya ovata bar kextract, citrus extract, Lonicera japonica (honeysuckle), polylysine, steviol glycosides

Warnings

- Stop use and ask your doctor if symptoms persist or worsen.
- If pregnant or breast-feeding, take only on advice of a healthcare professional.

- Keep out of reach of children.

Directions

- Initially, depress pump until primed.
- Spray one dose directly into mouth.
- Adults 12 and up: 3 sprays 3 times per day
- Children 2-12: 2 sprays 3 times per day
- Children 2 mo-2 yr. 1 spray 3 times per day

OTHER SAFETY INFORMATION

Tamper resistant for your protection. Use only if safety seal is intact. This product has not been clinically tested.

PURPOSE

Uses for fast relief of ileocecal valve symptoms:

- sensitivity, pain or pressure in lower right abdomen
- dark circles around eyes
- bad breath
- toxic taste in mouth
- ringing in ears
- toxic intestinal irritations

Note: Consult a physician for any severe abdominal pain.

.